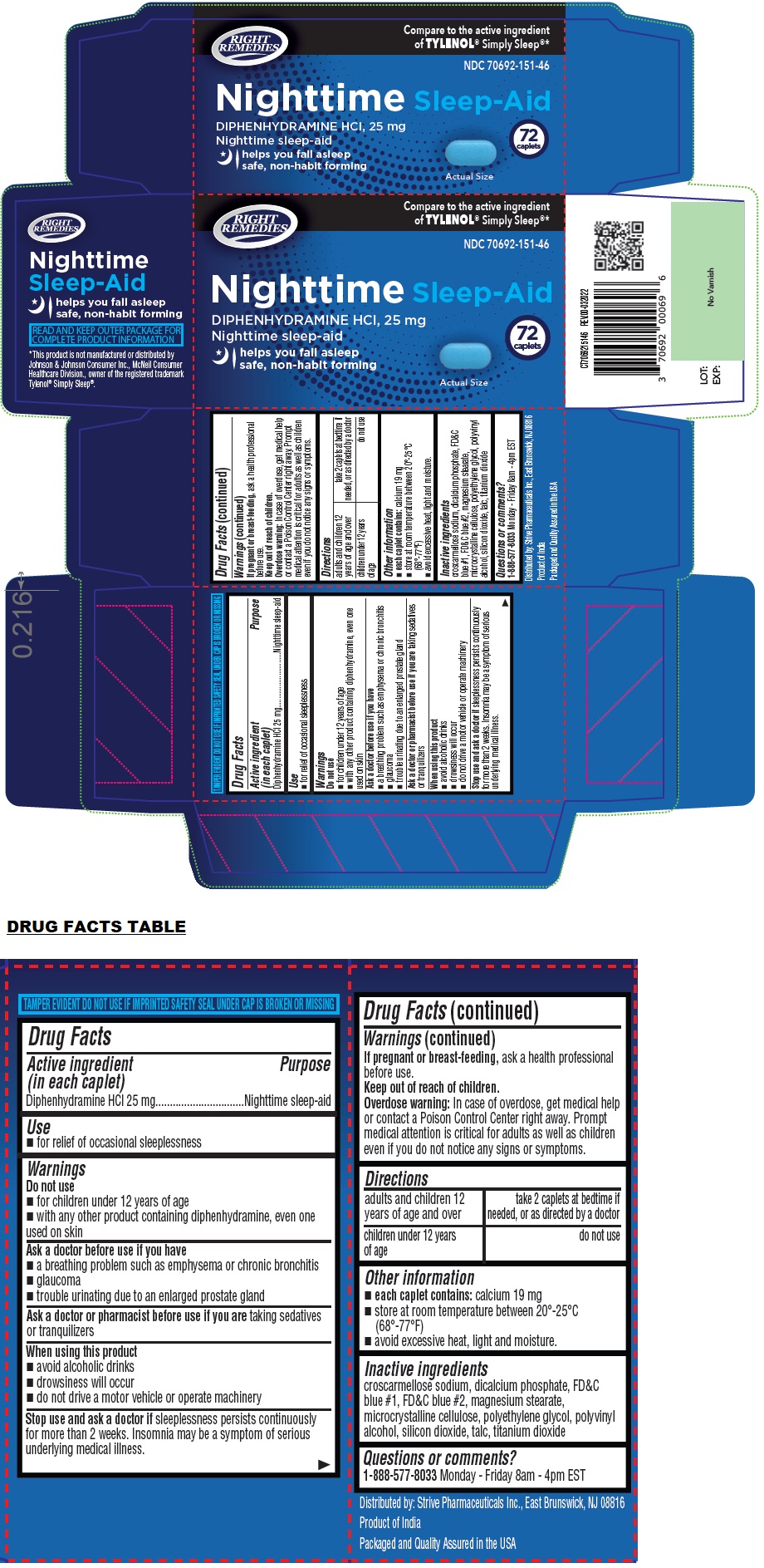 DRUG LABEL: Nighttime Sleep Aid
NDC: 70692-151 | Form: TABLET, COATED
Manufacturer: Strive Pharmaceuticals Inc.
Category: otc | Type: HUMAN OTC DRUG LABEL
Date: 20241211

ACTIVE INGREDIENTS: DIPHENHYDRAMINE HYDROCHLORIDE 25 mg/1 1
INACTIVE INGREDIENTS: CROSCARMELLOSE SODIUM; ANHYDROUS DIBASIC CALCIUM PHOSPHATE; FD&C BLUE NO. 1; FD&C BLUE NO. 2; MAGNESIUM STEARATE; MICROCRYSTALLINE CELLULOSE; POLYETHYLENE GLYCOL, UNSPECIFIED; POLYVINYL ALCOHOL, UNSPECIFIED; SILICON DIOXIDE; TALC; TITANIUM DIOXIDE

RIGHT REMEDIES Nighttime Sleep-Aid

Active ingredient (in each caplet)

Diphenhydramine HCl 25 mg

Purpose

Nighttime sleep-aid

Use

• for relief of occasional sleeplessness

Warnings

Do not use
• for children under 12 years of age
• with any other product containing diphenhydramine, even one used on skin

Ask a doctor before use if you have
• a breathing problem such as emphysema or chronic bronchitis
• glaucoma
• trouble urinating due to an enlarged prostate gland

Ask a doctor or pharmacist before use if you are taking sedatives or tranquilizers

When using this product
• avoid alcoholic drinks
• drowsiness will occur
• do not drive a motor vehicle or operate machinery

Stop use and ask a doctor if sleeplessness persists continuously for more than 2 weeks. Insomnia may be a symptom of serious underlying medical illness.

If pregnant or breast-feeding, ask a health professional before use.

Keep out of reach of children.
Overdose warning: In case of overdose, get medical help or contact a Poison Control Center right away. Prompt medical attention is critical for adults as well as children even if you do not notice any signs or symptoms.

Directions

adults and children 12 years of age and over | take 2 caplets at bedtime if needed, or as directed by a doctor
children under 12 years of age | do not use

Other information

• each caplet contains: calcium 19 mg
• store at room temperature between 20°-25°C (68°-77°F)
• avoid excessive heat, light and moisture.

Inactive ingredients

croscarmellose sodium, dicalcium phosphate, FD&C blue #1, FD&C blue #2, magnesium stearate, microcrystalline cellulose, polyethylene glycol, polyvinyl alcohol, silicon dioxide, talc, titanium dioxide

Questions or comments?

1-888-577-8033 Monday - Friday 8am - 4pm EST

RIGHT REMEDIES

Compare to the active ingredient of TYLENOL® Simply Sleep®*

helps you fall asleep
safe, non-habit forming

TAMPER EVIDENT DO NOT USE IF IMPRINTED SAFETY SEAL UNDER CAP IS BROKEN OR MISSING

Distributed by: Strive Pharmaceuticals Inc., East Brunswick, NJ 08816

Product of India

Packaged and Quality Assured in the USA

READ AND KEEP OUTER PACKAGE FOR COMPLETE PRODUCT INFORMATION

*This product is not manufactured or distributed by Johnson & Johnson Consumer Inc., McNeil Consumer Healthcare Division., owner of the registered trademark Tylenol® Simply Sleep®.

REV.00-032022